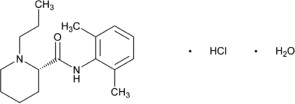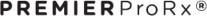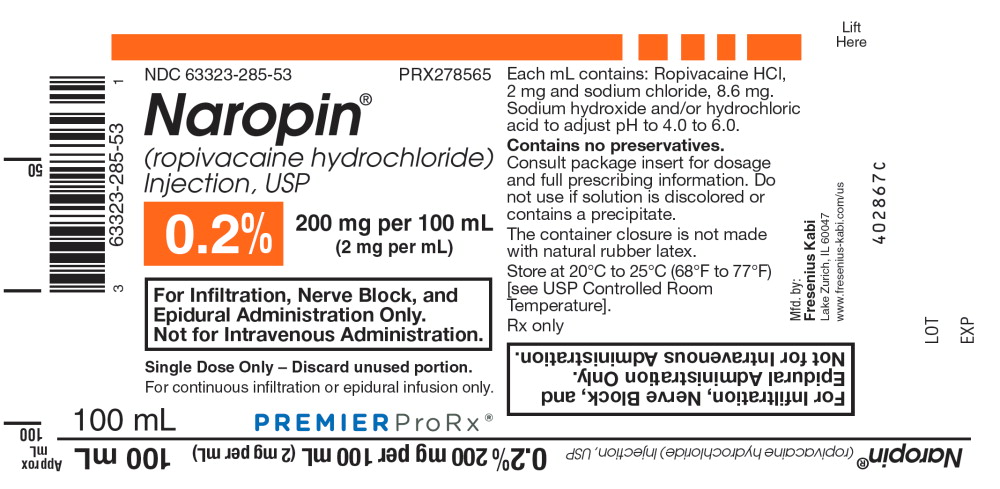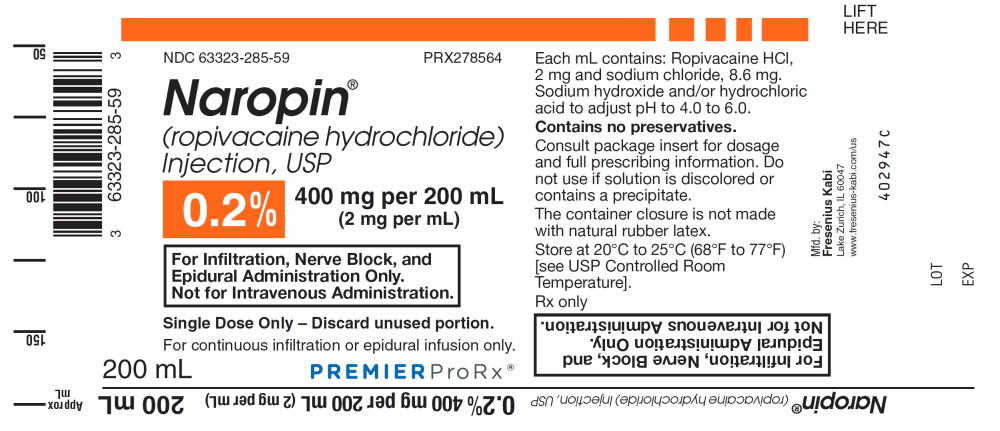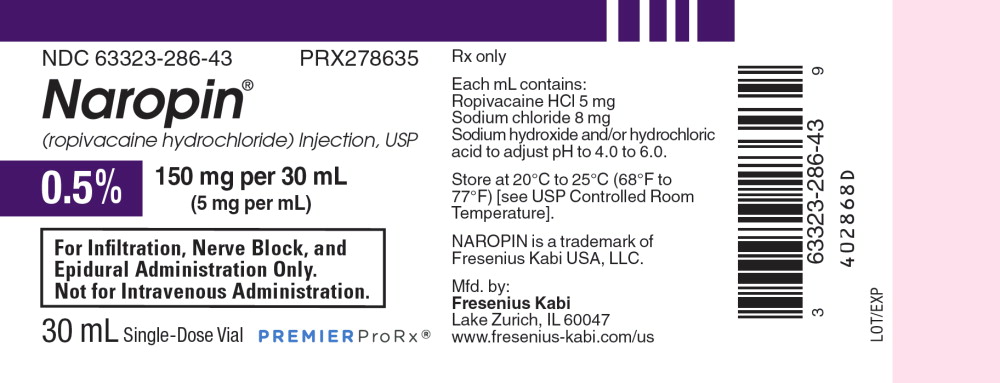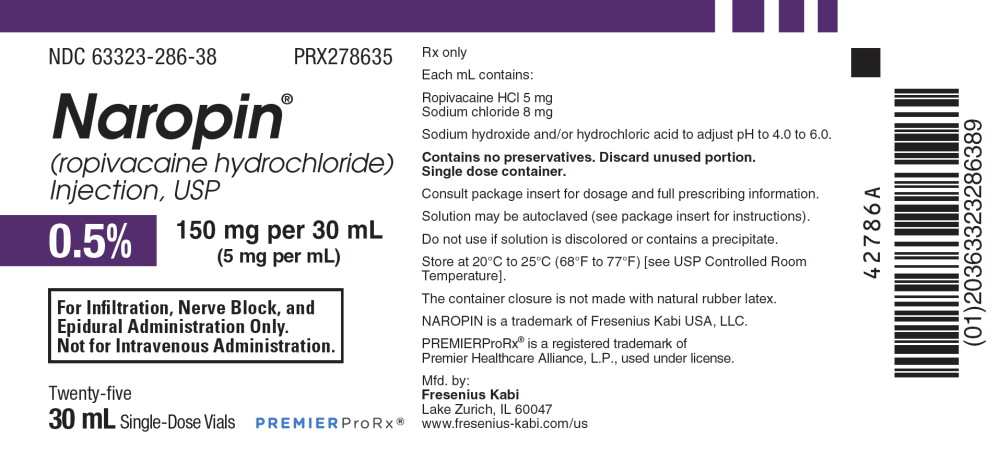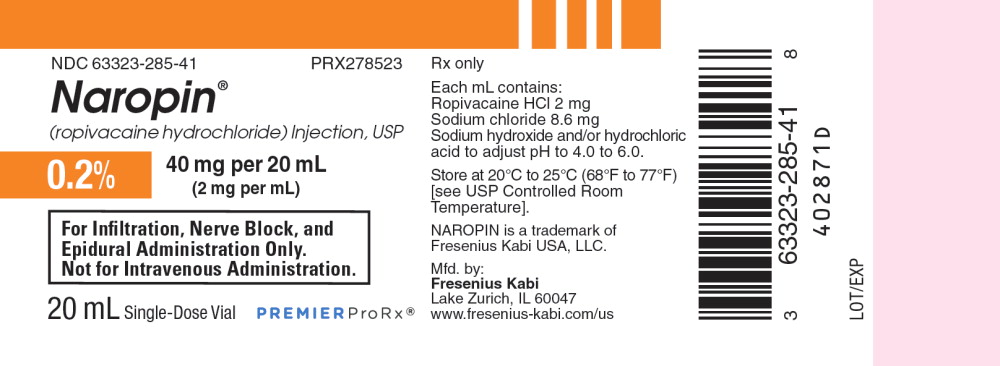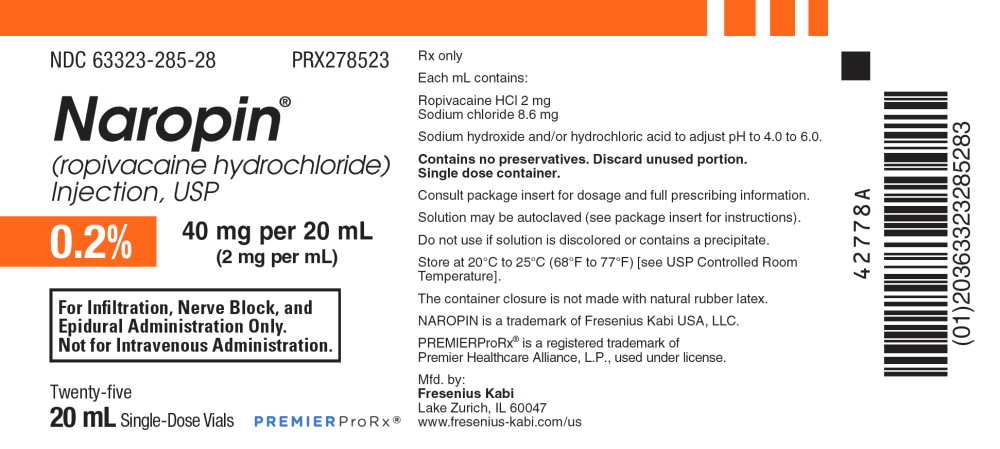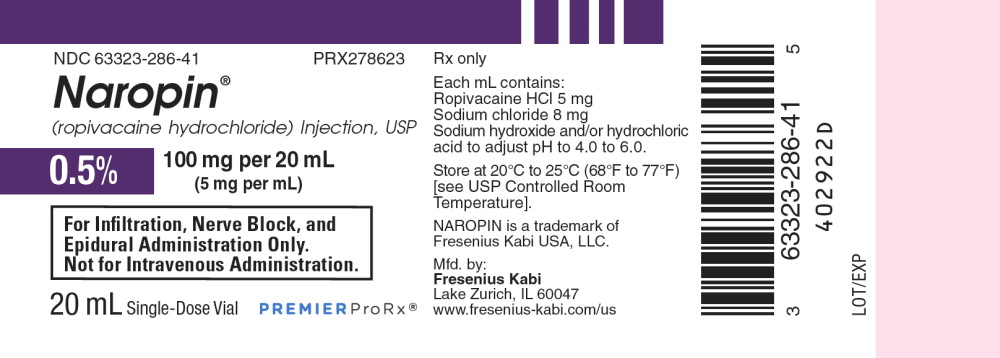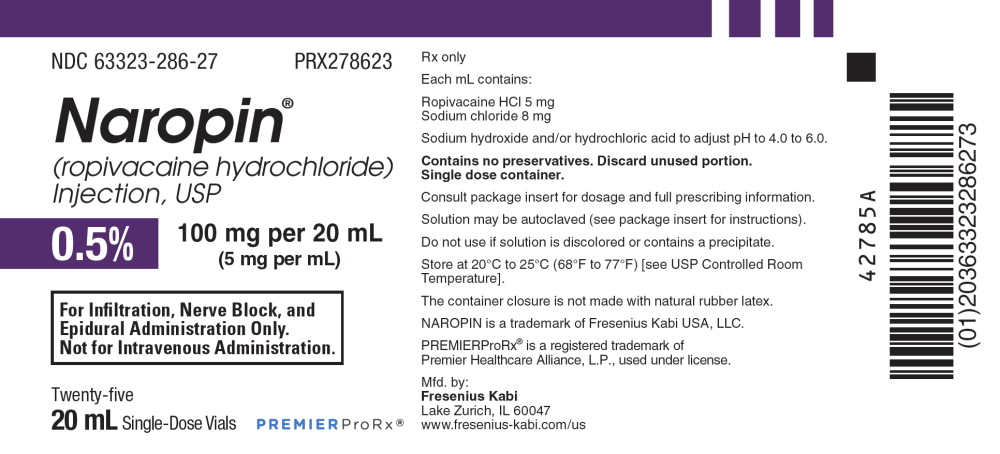 DRUG LABEL: Naropin
NDC: 63323-286 | Form: INJECTION, SOLUTION
Manufacturer: Fresenius Kabi USA, LLC

Category: prescription | Type: HUMAN PRESCRIPTION DRUG LABEL
Date: 20240815

ACTIVE INGREDIENTS: ROPIVACAINE HYDROCHLORIDE
 5 mg/1 mL
INACTIVE INGREDIENTS: SODIUM CHLORIDE 8 mg/1 mL; SODIUM HYDROXIDE; HYDROCHLORIC ACID

HIGHLIGHTS OF PRESCRIBING INFORMATION

These highlights do not include all the information needed to use NAROPIN® safely and effectively. See full prescribing information for NAROPIN®.
NAROPIN® (ropivacaine hydrochloride) injection, for epidural, perineural, or infiltration use
Initial U.S. Approval: 1996 Rx Only

1 INDICATIONS AND USAGE

NAROPIN is an amide local anesthetic indicated in adults for the production of local or regional anesthesia for surgery and for acute pain management.

Surgical Anesthesia: epidural block for surgery including cesarean section; major nerve block; local infiltration

Acute Pain Management: epidural continuous infusion or intermittent bolus, e.g., postoperative or labor; local infiltration

2 DOSAGE AND ADMINISTRATION

- See Table 1 for Dosage Recommendations (2.2)

3 DOSAGE FORMS AND STRENGTHS

- Injection: 2 mg/mL (0.2%) or 5 mg/mL (0.5%) in single-dose vials (3)
- Injection: 2 mg/mL (0.2%) in single-dose infusion bottles (3)

4 CONTRAINDICATIONS

History of hypersensitivity to local anesthetics of the amide type. (4)

5 WARNINGS AND PRECAUTIONS

- Delay in proper management of dose-related toxicity, underventilation, and/or altered sensitivity may lead to the development of acidosis, cardiac arrest and, possibly, death. (5.1)
- In performing NAROPIN blocks, unintended intravenous injection is possible and may result in cardiac arrhythmia or cardia arrest. (5.2)
- Intra-articular infusions of local anesthetics may cause chondrolysis. NAROPIN is not approved for this use. (5.3).
- Signs of methemoglobinemia may occur. (5.4)

6 ADVERSE REACTIONS

Most common adverse reactions (incidence ≥ 5%) are hypotension, nausea, vomiting, bradycardia, fever, pain, postoperative complications, anemia, paresthesia, headache, pruritus, and back pain. (6)

To report SUSPECTED ADVERSE REACTIONS, contact Fresenius Kabi USA, LLC at 1-800-551-7176 or FDA at 1-800-FDA-1088 or www.fda.gov/medwatch

7 DRUG INTERACTIONS

- Agents structurally related to amide-type local anesthetics: Concurrent use may cause additive effects. (7)

FULL PRESCRIBING INFORMATION

1 INDICATIONS AND USAGE

NAROPIN is indicated for the production of local or regional anesthesia for surgery and for acute pain management.

Surgical Anesthesia: epidural block for surgery including cesarean section; major nerve block; local infiltration

Acute Pain Management: epidural continuous infusion or intermittent bolus, e.g., postoperative or labor; local infiltration

2 DOSAGE AND ADMINISTRATION

2.1 Important Administration Instructions

There have been adverse event reports of chondrolysis in patients receiving intra-articular infusions of local anesthetics following arthroscopic and other surgical procedures. NAROPIN is not approved for this use [see Warnings and Precautions (5.3)].

The rapid injection of a large volume of local anesthetic solution should be avoided and fractional (incremental) doses should always be used. The smallest dose and concentration required to produce the desired result should be administered.

The dose of any local anesthetic administered varies with the anesthetic procedure, the area to be anesthetized, the vascularity of the tissues, the number of neuronal segments to be blocked, the depth of anesthesia and degree of muscle relaxation required, the duration of anesthesia desired, individual tolerance, and the physical condition of the patient. Patients in poor general condition due to aging or other compromising factors such as partial or complete heart conduction block, advanced liver disease or severe renal dysfunction require special attention although regional anesthesia is frequently indicated in these patients. To reduce the risk of potentially serious adverse reactions, attempts should be made to optimize the patient's condition before major blocks are performed, and the dosage should be adjusted accordingly.

Use an adequate test dose (3 to 5 mL of a short acting local anesthetic solution containing epinephrine) prior to induction of complete block. This test dose should be repeated if the patient is moved in such a fashion as to have displaced the epidural catheter. Allow adequate time for onset of anesthesia following administration of each test dose.

These products are intended for single dose and are free from preservatives. Any solution remaining from an opened container should be discarded promptly. In addition, continuous infusion bottles should not be left in place for more than 24 hours.

2.2 Dosage Recommendations

Table 1 Dosage Recommendations
 | Conc. |  | Volume | Dose | Onset min | Duration hours
 | mg/mL | (%) | mL | mg
SURGICAL ANESTHESIA
Lumbar Epidural | 5 | (0.5%) | 15 to 30 | 75 to 150 | 15 to 30 | 2 to 4
Administration | 7.5 | (0.75%) | 15 to 25 | 113 to 188 | 10 to 20 | 3 to 5
Surgery | 10 | (1%) | 15 to 20 | 150 to 200 | 10 to 20 | 4 to 6
Lumbar Epidural | 5 | (0.5%) | 20 to 30 | 100 to 150 | 15 to 25 | 2 to 4
Administration | 7.5 | (0.75%) | 15 to 20 | 113 to 150 | 10 to 20 | 3 to 5
Cesarean Section
Thoracic Epidural | 5 | (0.5%) | 5 to 15 | 25 to 75 | 10 to 20 | n/a*
Administration | 7.5 | (0.75%) | 5 to 15 | 38 to 113 | 10 to 20 | n/a*
Surgery
Major Nerve Block† | 5 | (0.5%) | 35 to 50 | 175 to 250 | 15 to 30 | 5 to 8
(e.g., brachial plexus block) | 7.5 | (0.75%) | 10 to 40 | 75 to 300 | 10 to 25 | 6 to 10
Field Block | 5 | (0.5%) | 1 to 40 | 5 to 200 | 1 to 15 | 2 to 6
(e.g., minor nerve blocks and
infiltration)
LABOR PAIN MANAGEMENT
Lumbar Epidural Administration
Initial Dose | 2 | (0.2%) | 10 to 20 | 20 to 40 | 10 to15 | 0.5 to 1.5
Continuous infusion‡ | 2 | (0.2%) | 6 to 14 mL/h | 12 to 28 mg/h | n/a* | n/a*
Incremental injections (top-up)‡ | 2 | (0.2%) | 10 to 15 mL/h | 20 to 30 mg/h | n/a* | n/a*
POSTOPERATIVE PAIN MANAGEMENT
Lumbar Epidural Administration
Continuous infusion§ | 2 | (0.2%) | 6 to 14 mL/h | 12 to 28 mg/h | n/a* | n/a*
Thoracic Epidural | 2 | (0.2%) | 6 to 14 mL/h | 12 to 28 mg/h | n/a* | n/a*
Administration
Continuous infusion§
Infiltration | 2 | (0.2%) | 1 to 100 | 2 to 200 | 1 to 5 | 2 to 6
(e.g., minor nerve block) | 5 | (0.5%) | 1 to 40 | 5 to 200 | 1 to 5 | 2 to 6
* = Not Applicable
† = The dose for a major nerve block must be adjusted according to site of administration and patient status. Supraclavicular brachial plexus blocks may be associated with a higher frequency of serious adverse reactions, regardless of the local anesthetic used [see Warnings and Precautions (5.7)].
‡ = Median dose of 21 mg per hour was administered by continuous infusion or by incremental injections (top-ups) over a median delivery time of 5.5 hours.
§ = Cumulative doses up to 770 mg of NAROPIN over 24 hours (intraoperative block plus postoperative infusion); Continuous epidural infusion at rates up to 28 mg per hour for 72 hours have been well tolerated in adults, i.e., 2016 mg plus surgical dose of approximately 100 to 150 mg as top-up.

The doses in the table are those considered to be necessary to produce a successful block and should be regarded as guidelines for use in adults. Individual variations in onset and duration occur. The figures reflect the expected average dose range needed. For other local anesthetic techniques standard current textbooks should be consulted.

When prolonged blocks are used, either through continuous infusion or through repeated bolus administration, the risks of reaching a toxic plasma concentration or inducing local neural injury must be considered. Experience to date indicates that a cumulative dose of up to 770 mg NAROPIN administered over 24 hours is well tolerated in adults when used for postoperative pain management: i.e., 2016 mg. Caution should be exercised when administering NAROPIN for prolonged periods of time, e.g., >70 hours in debilitated patients.

For treatment of postoperative pain, the following technique can be recommended: If regional anesthesia was not used intraoperatively, then an initial epidural block with 5 to 7 mL NAROPIN is induced via an epidural catheter. Analgesia is maintained with an infusion of NAROPIN, 2 mg/mL (0.2%). Clinical studies have demonstrated that infusion rates of 6 to 14 mL (12 to 28 mg) per hour provide adequate analgesia with nonprogressive motor block. With this technique a significant reduction in the need for opioids was demonstrated. Clinical experience supports the use of NAROPIN epidural infusions for up to 72 hours.

2.3 Other Administration Considerations

Disinfecting agents containing heavy metals, which cause release of respective ions (mercury, zinc, copper, etc.) should not be used for skin or mucous membrane disinfection since they have been related to incidents of swelling and edema.

When chemical disinfection of the container surface is desired, either isopropyl alcohol (91%) or ethyl alcohol (70%) is recommended. It is recommended that chemical disinfection be accomplished by wiping the polypropylene ampule or vial stopper thoroughly with cotton or gauze that has been moistened with the recommended alcohol just prior to use. When a container is required to have a sterile outside, a Sterile-Pak should be chosen. Glass containers may, as an alternative, be autoclaved once. Stability has been demonstrated using a targeted F0 of 7 minutes at 121°C.

The solubility of ropivacaine is limited at pH above 6. Thus, care must be taken as precipitation may occur if NAROPIN is mixed with alkaline solutions. Parenteral drug products should be inspected visually for particulate matter and discoloration prior to administration, whenever solution and container permit. Solutions which are discolored or which contain particulate matter should not be administered.

3 DOSAGE FORMS AND STRENGTHS

NAROPIN® (ropivacaine hydrochloride) injection is a clear, colorless, preservative-free solution available as:

NAROPIN® Single Dose Vials

- 0.2%, 40 mg per 20 mL (2 mg/mL), in 20 mL single-dose vial
- 0.5%, 100 mg per 20 mL (5 mg/mL), 20 mL single-dose vial
- 0.5%, 150 mg per 30 mL (5 mg/mL), 30 mL single-dose vial

NAROPIN® Single Dose Infusion Bottles

- 0.2%, 200 mg per 100 mL (2 mg/mL), 100 mL single-dose infusion bottle
- 0.2%, 400 mg per 200 mL (2 mg/mL), 200 mL single-dose infusion bottle

4 CONTRAINDICATIONS

NAROPIN is contraindicated in patients with a known hypersensitivity to ropivacaine or to any local anesthetic agent of the amide type.

5 WARNINGS AND PRECAUTIONS

5.1 General Warnings and Precautions

Prior to receiving major blocks the general condition of the patient should be optimized and the patient should have an IV line inserted. All necessary precautions should be taken to avoid intravascular injection. Local anesthetics should only be administered by clinicians who are well versed in the diagnosis and management of dose-related toxicity and other acute emergencies which might arise from the block to be employed, and then only after insuring the immediate (without delay) availability of oxygen, other resuscitative drugs, cardiopulmonary resuscitative equipment, and the personnel resources needed for proper management of toxic reactions and related emergencies [see Adverse Reactions (6) and Overdosage (10.1)]. Delay in proper management of dose-related toxicity, underventilation from any cause, and/or altered sensitivity may lead to the development of acidosis, cardiac arrest and, possibly, death.

The safe and effective use of local anesthetics depends on proper dosage, correct technique, adequate precautions and readiness for emergencies.

Resuscitative equipment, oxygen and other resuscitative drugs should be available for immediate use [see Adverse Reactions (6)]. The lowest dosage that results in effective anesthesia should be used to avoid high plasma levels and serious adverse events. Injections should be made slowly and incrementally, with frequent aspirations before and during the injection to avoid intravascular injection. When a continuous catheter technique is used, syringe aspirations should also be performed before and during each supplemental injection. During the administration of epidural anesthesia, it is recommended that a test dose of a local anesthetic with a fast onset be administered initially and that the patient be monitored for central nervous system and cardiovascular toxicity, as well as for signs of unintended intrathecal administration before proceeding. When clinical conditions permit, consideration should be given to employing local anesthetic solutions, which contain epinephrine for the test dose because circulatory changes compatible with epinephrine may also serve as a warning sign of unintended intravascular injection. An intravascular injection is still possible even if aspirations for blood are negative. Administration of higher than recommended doses of NAROPIN to achieve greater motor blockade or increased duration of sensory blockade may result in cardiovascular depression, particularly in the event of inadvertent intravascular injection. Tolerance to elevated blood levels varies with the physical condition of the patient. Debilitated, elderly patients and acutely ill patients should be given reduced doses commensurate with their age and physical condition. Local anesthetics should also be used with caution in patients with hypotension, hypovolemia or heart block.

Solutions of NAROPIN should not be used for the production of obstetrical paracervical block anesthesia, retrobulbar block, or spinal anesthesia (subarachnoid block) due to insufficient data to support such use. Intravenous regional anesthesia (bier block) should not be performed due to a lack of clinical experience and the risk of attaining toxic blood levels of ropivacaine.

It is essential that aspiration for blood, or cerebrospinal fluid (where applicable), be done prior to injecting any local anesthetic, both the original dose and all subsequent doses, to avoid intravascular or subarachnoid injection. However, a negative aspiration does not ensure against an intravascular or subarachnoid injection.

5.2 Unintended Intravenous Injection

In performing NAROPIN blocks, unintended intravenous injection is possible and may result in cardiac arrhythmia or cardiac arrest. The potential for successful resuscitation has not been studied in humans. There have been rare reports of cardiac arrest during the use of NAROPIN for epidural anesthesia or peripheral nerve blockade, the majority of which occurred after unintentional accidental intravascular administration in elderly patients and in patients with concomitant heart disease. In some instances, resuscitation has been difficult. Should cardiac arrest occur, prolonged resuscitative efforts may be required to improve the probability of a successful outcome.

NAROPIN should be administered in incremental doses. It is not recommended for emergency situations, where a fast onset of surgical anesthesia is necessary. Historically, pregnant patients were reported to have a high risk for cardiac arrhythmias, cardiac/circulatory arrest and death when 0.75% bupivacaine (another member of the amino amide class of local anesthetics) was inadvertently rapidly injected intravenously.

5.3 Intra-Articular Infusions and Risk of Chondrolysis

Intra-articular infusions of local anesthetics following arthroscopic and other surgical procedures is an unapproved use, and there have been post-marketing reports of chondrolysis in patients receiving such infusions. The majority of reported cases of chondrolysis have involved the shoulder joint; cases of gleno-humeral chondrolysis have been described in pediatric and adult patients following intra-articular infusions of local anesthetics with and without epinephrine for periods of 48 to 72 hours. There is insufficient information to determine whether shorter infusion periods are not associated with these findings. The time of onset of symptoms, such as joint pain, stiffness and loss of motion can be variable, but may begin as early as the 2nd month after surgery. Currently, there is no effective treatment for chondrolysis; patients who experienced chondrolysis have required additional diagnostic and therapeutic procedures and some required arthroplasty or shoulder replacement.

5.4 Risk of Methemoglobinemia

Cases of methemoglobinemia have been reported in association with local anesthetic use. Although all patients are at risk for methemoglobinemia, patients with glucose-6-phosphate dehydrogenase deficiency, congenital or idiopathic methemoglobinemia, cardiac or pulmonary compromise, infants under 6 months of age, and concurrent exposure to oxidizing agents or their metabolites are more susceptible to developing clinical manifestations of the condition. If local anesthetics must be used in these patients, close monitoring for symptoms and signs of methemoglobinemia is recommended.

Signs of methemoglobinemia may occur immediately or may be delayed some hours after exposure, and are characterized by a cyanotic skin discoloration and/or abnormal coloration of the blood. Methemoglobin levels may continue to rise; therefore, immediate treatment is required to avert more serious central nervous system and cardiovascular adverse effects, including seizures, coma, arrhythmias, and death. Discontinue NAROPIN and any other oxidizing agents. Depending on the severity of the signs and symptoms, patients may respond to supportive care, i.e., oxygen therapy, hydration. A more severe clinical presentation may require treatment with methylene blue, exchange transfusion, or hyperbaric oxygen.

5.5 Central Nervous System Toxicity

Careful and constant monitoring of cardiovascular and respiratory vital signs (adequacy of ventilation) and the patient's state of consciousness should be performed after each local anesthetic injection. It should be kept in mind at such times that restlessness, anxiety, incoherent speech, light-headedness, numbness and tingling of the mouth and lips, metallic taste, tinnitus, dizziness, blurred vision, tremors, twitching, depression, or drowsiness may be early warning signs of central nervous system toxicity.

5.6 Epidural Anesthesia

A well-known risk of epidural anesthesia may be an unintentional subarachnoid injection of local anesthetic. Two clinical studies have been performed to verify the safety of NAROPIN at a volume of 3 mL injected into the subarachnoid space since this dose represents an incremental epidural volume that could be unintentionally injected. The 15 and 22.5 mg doses injected resulted in sensory levels as high as T5 and T4, respectively. Anesthesia to pinprick started in the sacral dermatomes in 2 to 3 minutes, extended to the T10 level in 10 to 13 minutes and lasted for approximately 2 hours. The results of these two clinical studies showed that a 3 mL dose did not produce any serious adverse events when spinal anesthesia blockade was achieved.

During epidural administration, NAROPIN should be administered in incremental doses of 3 to 5 mL with sufficient time between doses to detect toxic manifestations of unintentional intravascular or intrathecal injection. Syringe aspirations should also be performed before and during each supplemental injection in continuous (intermittent) catheter techniques. An intravascular injection is still possible even if aspirations for blood are negative. During the administration of epidural anesthesia, it is recommended that a test dose be administered initially and the effects monitored before the full dose is given. When clinical conditions permit, the test dose should contain an appropriate dose of epinephrine to serve as a warning of unintentional intravascular injection. If injected into a blood vessel, this amount of epinephrine is likely to produce a transient "epinephrine response" within 45 seconds, consisting of an increase in heart rate and systolic blood pressure, circumoral pallor, palpitations and nervousness in the unsedated patient. The sedated patient may exhibit only a pulse rate increase of 20 or more beats per minute for 15 or more seconds. Therefore, following the test dose, the heart should be continuously monitored for a heart rate increase. Patients on beta-blockers may not manifest changes in heart rate, but blood pressure monitoring can detect a rise in systolic blood pressure. A test dose of a short-acting amide anesthetic such as lidocaine is recommended to detect an unintentional intrathecal administration. This will be manifested within a few minutes by signs of spinal block (e.g., decreased sensation of the buttocks, paresis of the legs, or, in the sedated patient, absent knee jerk). An intravascular or subarachnoid injection is still possible even if results of the test dose are negative. The test dose itself may produce a systemic toxic reaction, high spinal or epinephrine-induced cardiovascular effects.

5.7 Use in Brachial Plexus Block

Ropivacaine plasma concentrations may approach the threshold for central nervous system toxicity after the administration of 300 mg of ropivacaine for brachial plexus block. Caution should be exercised when using the 300 mg dose [see Overdosage (10)].

The dose for a major nerve block must be adjusted according to the site of administration and patient status. Supraclavicular brachial plexus blocks may be associated with a higher frequency of serious adverse reactions, regardless of the local anesthetic used.

5.8 Use in Peripheral Nerve Block

Major peripheral nerve blocks may result in the administration of a large volume of local anesthetic in highly vascularized areas, often close to large vessels where there is an increased risk of intravascular injection and/or rapid systemic absorption, which can lead to high plasma concentrations.

5.9 Use in Head and Neck Area

Small doses of local anesthetics injected into the head and neck area may produce adverse reactions similar to systemic toxicity seen with unintentional intravascular injections of larger doses. The injection procedures require the utmost care. Confusion, convulsions, respiratory depression, and/or respiratory arrest, and cardiovascular stimulation or depression have been reported. These reactions may be due to intra-arterial injection of the local anesthetic with retrograde flow to the cerebral circulation. Patients receiving these blocks should have their circulation and respiration monitored and be constantly observed. Resuscitative equipment and personnel for treating adverse reactions should be immediately available. Dosage recommendations should not be exceeded [see Dosage and Administration (2.2)].

5.10 Use in Ophthalmic Surgery

The use of NAROPIN in retrobulbar blocks for ophthalmic surgery has not been studied. Until appropriate experience is gained, the use of NAROPIN for such surgery is not recommended.

5.11 Hepatic Disease

Because amide-type local anesthetics such as ropivacaine are metabolized by the liver, these drugs, especially repeat doses, should be used cautiously in patients with hepatic disease. Patients with severe hepatic disease, because of their inability to metabolize local anesthetics normally, are at a greater risk of developing toxic plasma concentrations.

5.12 Cardiovascular Impairment

Local anesthetics should also be used with caution in patients with impaired cardiovascular function because they may be less able to compensate for functional changes associated with the prolongation of A-V conduction produced by these drugs.

5.13 Risk of Additive Effects

NAROPIN should be used with caution in patients receiving other local anesthetics or agents structurally related to amide- type local anesthetics, since the toxic effects of these drugs are additive. [See Drug Interactions 7.0]

Patients treated with class III antiarrhythmic drugs (e.g., amiodarone) should be under close surveillance and ECG monitoring considered, since cardiac effects may be additive. [See Drug Interactions 7.0]

5.14 Malignant Hyperthermia

Many drugs used during the conduct of anesthesia are considered potential triggering agents for malignant hyperthermia (MH). Amide-type local anesthetics are not known to trigger this reaction. However, since the need for supplemental general anesthesia cannot be predicted in advance, it is suggested that a standard protocol for MH management should be available.

6 ADVERSE REACTIONS

Reactions to ropivacaine are characteristic of those associated with other amide-type local anesthetics. A major cause of adverse reactions to this group of drugs may be associated with excessive plasma levels, which may be due to overdosage, unintentional intravascular injection or slow metabolic degradation.

The reported adverse events are derived from clinical studies conducted in the U.S. and other countries. The reference drug was usually bupivacaine. The studies used a variety of premedications, sedatives, and surgical procedures of varying length. A total of 3,988 patients have been exposed to NAROPIN at concentrations up to 1% in clinical trials. Each patient was counted once for each type of adverse event.

Because clinical trials are conducted under widely conditions, adverse reactions rates observed in the clinical trials of a drug cannot be directly compared to rates in the clinical trials of another drug and may not reflect the rates observed in practice.

Incidence ≥ 5%

For the indications of epidural administration in surgery, cesarean section, postoperative pain management, peripheral nerve block, and local infiltration, the following treatment-emergent adverse events were reported with an incidence of ≥ 5% in all clinical studies (N=3988): hypotension (37%), nausea (24.8%), vomiting (11.6%), bradycardia (9.3%), fever (9.2%), pain (8%), postoperative complications (7.1%), anemia (6.1%), paresthesia (5.6%), headache (5.1%), pruritus (5.1%), and back pain (5%).

Incidence 1 to 5%

Urinary retention, dizziness, rigors, hypertension, tachycardia, anxiety, oliguria, hypoesthesia, chest pain, hypokalemia, dyspnea, cramps, and urinary tract infection.

Incidence in Controlled Clinical Trials

The reported adverse events are derived from controlled clinical studies with NAROPIN (concentrations ranged from 0.125% to 1% for NAROPIN and 0.25% to 0.75% for bupivacaine) in the U.S. and other countries involving 3,094 patients. Table 2 and Table 3 list adverse events (number and percentage) that occurred in at least 1% of NAROPIN-treated patients in these studies. The majority of patients receiving concentrations higher than 5 mg/mL (0.5%) were treated with NAROPIN.

Table 2 Adverse Events Reported in ≥1% of Adult Patients Receiving Regional or Local Anesthesia (Surgery, Labor, Cesarean Section, Postoperative Pain Management, Peripheral Nerve Block and Local Infiltration)
 | NAROPIN total N=1661 |  | Bupivacaine total N=1433
Adverse Reaction | N | % | N | %
Hypotension | 536 | (32.3) | 408 | (28.5)
Nausea | 283 | (17) | 207 | (14.4)
Vomiting | 117 | (7) | 88 | (6.1)
Bradycardia | 96 | (5.8) | 73 | (5.1)
Headache | 84 | (5.1) | 68 | (4.7)
Paresthesia | 82 | (4.9) | 57 | (4)
Back pain | 73 | (4.4) | 75 | (5.2)
Pain | 71 | (4.3) | 71 | (5)
Pruritus | 63 | (3.8) | 40 | (2.8)
Fever | 61 | (3.7) | 37 | (2.6)
Dizziness | 42 | (2.5) | 23 | (1.6)
Rigors (Chills) | 42 | (2.5) | 24 | (1.7)
Postoperative complications | 41 | (2.5) | 44 | (3.1)
Hypoesthesia | 27 | (1.6) | 24 | (1.7)
Urinary retention | 23 | (1.4) | 20 | (1.4)
Progression of labor poor/failed | 23 | (1.4) | 22 | (1.5)
Anxiety | 21 | (1.3) | 11 | (0.8)
Breast disorder, breast-feeding | 21 | (1.3) | 12 | (0.8)
Rhinitis | 18 | (1.1) | 13 | (0.9)

Table 3 Adverse Events Reported in ≥1% of Fetuses or Neonates of Mothers Who Received Regional Anesthesia (Cesarean Section and Labor Studies)
 | NAROPIN total N = 639 |  | Bupivacaine total N = 573
Adverse Reaction | N | % | N | %
Fetal bradycardia | 77 | (12.1) | 68 | (11.9)
Neonatal jaundice | 49 | (7.7) | 47 | (8.2)
Neonatal complication-NOS | 42 | (6.6) | 38 | (6.6)
Apgar score low | 18 | (2.8) | 14 | (2.4)
Neonatal respiratory disorder | 17 | (2.7) | 18 | (3.1)
Neonatal tachypnea | 14 | (2.2) | 15 | (2.6)
Neonatal fever | 13 | (2) | 14 | (2.4)
Fetal tachycardia | 13 | (2) | 12 | (2.1)
Fetal distress | 11 | (1.7) | 10 | (1.7)
Neonatal infection | 10 | (1.6) | 8 | (1.4)
Neonatal hypoglycemia | 8 | (1.3) | 16 | (2.8)

Incidence <1%

The following adverse events were reported during the NAROPIN clinical program in more than one patient (N=3988), occurred at an overall incidence of <1%, and were considered relevant:

Application Site Reactions - injection site pain

Cardiovascular System - vasovagal reaction, syncope, postural hypotension, non-specific ECG abnormalities

Female Reproductive - poor progression of labor, uterine atony

Gastrointestinal System - fecal incontinence, tenesmus, neonatal vomiting

General and Other Disorders - hypothermia, malaise, asthenia, accident and/or injury

Hearing and Vestibular - tinnitus, hearing abnormalities

Heart Rate and Rhythm - extrasystoles, non-specific arrhythmias, atrial fibrillation

Liver and Biliary System - jaundice

Metabolic Disorders - hypomagnesemia

Musculoskeletal System - myalgia

Myo/Endo/Pericardium - ST segment changes, myocardial infarction

Nervous System - tremor, Horner's syndrome, paresis, dyskinesia, neuropathy, vertigo, coma, convulsion, hypokinesia, hypotonia, ptosis, stupor

Psychiatric Disorders - agitation, confusion, somnolence, nervousness, amnesia, hallucination, emotional lability, insomnia, nightmares

Respiratory System - bronchospasm, coughing

Skin Disorders - rash, urticaria

Urinary System Disorders - urinary incontinence, micturition disorder

Vascular - deep vein thrombosis, phlebitis, pulmonary embolism

Vision - vision abnormalities

For the indication epidural anesthesia for surgery, the 15 most common adverse events were compared between different concentrations of NAROPIN and bupivacaine. Table 4 is based on data from trials in the U.S. and other countries where NAROPIN was administered as an epidural anesthetic for surgery.

Table 4 Common Events (Epidural Administration)
Adverse Reaction | NAROPIN |  |  |  |  |  | Bupivacaine
Adverse Reaction | 5 mg/mL total N=256 |  | 7.5 mg/mL total N=297 |  | 10 mg/mL total N=207 |  | 5 mg/mL total N=236 |  | 7.5 mg/mL total N=174
 | N | (%) | N | (%) | N | (%) | N | (%) | N | (%)
hypotension | 99 | (38.7) | 146 | (49.2) | 113 | (54.6) | 91 | (38.6) | 89 | (51.1)
nausea | 34 | (13.3) | 68 | (22.9) |  |  | 41 | (17.4) | 36 | (20.7)
bradycardia | 29 | (11.3) | 58 | (19.5) | 40 | (19.3) | 32 | (13.6) | 25 | (14.4)
back pain | 18 | (7) | 23 | (7.7) | 34 | (16.4) | 21 | (8.9) | 23 | (13.2)
vomiting | 18 | (7) | 33 | (11.1) | 23 | (11.1) | 19 | (8.1) | 14 | (8)
headache | 12 | (4.7) | 20 | (6.7) | 16 | (7.7) | 13 | (5.5) | 9 | (5.2)
fever | 8 | (3.1) | 5 | (1.7) | 18 | (8.7) | 11 | (4.7)
chills | 6 | (2.3) | 7 | (2.4) | 6 | (2.9) | 4 | (1.7) | 3 | (1.7)
urinary retention | 5 | (2) | 8 | (2.7) | 10 | (4.8) | 10 | (4.2)
paresthesia | 5 | (2) | 10 | (3.4) | 5 | (2.4) | 7 | (3)
pruritus |  |  | 14 | (4.7) | 3 | (1.4) |  |  | 7 | (4)

Using data from the same studies, the number (%) of patients experiencing hypotension is displayed by patient age, drug and concentration in Table 5. In Table 6, the adverse events for NAROPIN are broken down by gender.

Table 5 Effects of Age on Hypotension (Epidural Administration) Total N: NAROPIN = 760, Bupivacaine = 410
 | NAROPIN |  |  |  |  |  | Bupivacaine
AGE | 5 mg/mL |  | 7.5 mg/mL |  | 10 mg/mL |  | 5 mg/mL |  | 7.5 mg/mL
 | N | (%) | N | (%) | N | (%) | N | (%) | N | (%)
< 65 | 68 | (32.2) | 99 | (43.2) | 87 | (51.5) | 64 | (33.5) | 73 | (48.3)
≥ 65 | 31 | (68.9) | 47 | (69.1) | 26 | (68.4) | 27 | (60) | 16 | (69.6)

Table 6 Most Common Adverse Events by Gender (Epidural Administration) Total N: Females = 405, Males = 355
 | Female |  | Male
Adverse Reaction | N | (%) | N | (%)
hypotension | 220 | (54.3) | 138 | (38.9)
nausea | 119 | (29.4) | 23 | (6.5)
bradycardia | 65 | (16) | 56 | (15.8)
vomiting | 59 | (14.6) | 8 | (2.3)
back pain | 41 | (10.1) | 23 | (6.5)
headache | 33 | (8.1) | 17 | (4.8)
chills | 18 | (4.4) | 5 | (1.4)
fever | 16 | (4) | 3 | (0.8)
pruritus | 16 | (4) | 1 | (0.3)
pain | 12 | (3) | 4 | (1.1)
urinary retention | 11 | (2.7) | 7 | (2)
dizziness | 9 | (2.2) | 4 | (1.1)
hypoesthesia | 8 | (2) | 2 | (0.6)
paresthesia | 8 | (2) | 10 | (2.8)

Systemic Reactions

The most commonly encountered acute adverse experiences that demand immediate countermeasures are related to the central nervous system and the cardiovascular system. These adverse experiences are generally dose-related and due to high plasma levels that may result from overdosage, rapid absorption from the injection site, diminished tolerance or from unintentional intravascular injection of the local anesthetic solution. In addition to systemic dose-related toxicity, unintentional subarachnoid injection of drug during the intended performance of lumbar epidural block or nerve blocks near the vertebral column (especially in the head and neck region) may result in underventilation or apnea ("Total or High Spinal"). Also, hypotension due to loss of sympathetic tone and respiratory paralysis or underventilation due to cephalad extension of the motor level of anesthesia may occur. This may lead to secondary cardiac arrest if untreated. Factors influencing plasma protein binding, such as acidosis, systemic diseases that alter protein production or competition with other drugs for protein binding sites, may diminish individual tolerance.

Epidural administration of NAROPIN has, in some cases, as with other local anesthetics, been associated with transient increases in temperature to > 38.5°C. This occurred more frequently at doses of NAROPIN > 16 mg/h.

Neurologic Reactions

These are characterized by excitation and/or depression. Restlessness, anxiety, dizziness, tinnitus, blurred vision or tremors may occur, possibly proceeding to convulsions. However, excitement may be transient or absent, with depression being the first manifestation of an adverse reaction. This may quickly be followed by drowsiness merging into unconsciousness and respiratory arrest. Other central nervous system effects may be nausea, vomiting, chills, and constriction of the pupils.

The incidence of convulsions associated with the use of local anesthetics varies with the route of administration and the total dose administered. In a survey of studies of epidural anesthesia, overt toxicity progressing to convulsions occurred in approximately 0.1% of local anesthetic administrations.

The incidence of adverse neurological reactions associated with the use of local anesthetics may be related to the total dose and concentration of local anesthetic administered and are also dependent upon the particular drug used, the route of administration, and the physical status of the patient. Many of these observations may be related to local anesthetic techniques, with or without a contribution from the drug. During lumbar epidural block, occasional unintentional penetration of the subarachnoid space by the catheter or needle may occur. Subsequent adverse effects may depend partially on the amount of drug administered intrathecally as well as the physiological and physical effects of a dural puncture. These observations may include spinal block of varying magnitude (including high or total spinal block), hypotension secondary to spinal block, urinary retention, loss of bladder and bowel control (fecal and urinary incontinence), and loss of perineal sensation and sexual function. Signs and symptoms of subarachnoid block typically start within 2 to 3 minutes of injection. Doses of 15 and 22.5 mg of NAROPIN resulted in sensory levels as high as T5 and T4, respectively. Analgesia started in the sacral dermatomes in 2 to 3 minutes and extended to the T10 level in 10 to 13 minutes and lasted for approximately 2 hours. Other neurological effects following unintentional subarachnoid administration during epidural anesthesia may include persistent anesthesia, paresthesia, weakness, paralysis of the lower extremities, and loss of sphincter control; all of which may have slow, incomplete or no recovery. Headache, septic meningitis, meningismus, slowing of labor, increased incidence of forceps delivery, or cranial nerve palsies due to traction on nerves from loss of cerebrospinal fluid have been reported [see Dosage and Administration (2.1)]. A high spinal is characterized by paralysis of the arms, loss of consciousness, respiratory paralysis and bradycardia.

Cardiovascular System Reactions

High doses or unintentional intravascular injection may lead to high plasma levels and related depression of the myocardium, decreased cardiac output, heart block, hypotension, bradycardia, ventricular arrhythmias, including ventricular tachycardia and ventricular fibrillation, and possibly cardiac arrest [see Warnings and Precautions (5.2) and Overdosage (10)].

Allergic Reactions

Allergic type reactions are rare and may occur as a result of sensitivity to the local anesthetic [see Warnings and Precautions (5.1)]. These reactions are characterized by signs such as urticaria, pruritus, erythema, angioneurotic edema (including laryngeal edema), tachycardia, sneezing, nausea, vomiting, dizziness, syncope, excessive sweating, elevated temperature, and possibly, anaphylactoid symptomatology (including severe hypotension). Cross-sensitivity among members of the amide- type local anesthetic group has been reported. The usefulness of screening for sensitivity has not been definitively established.

7 DRUG INTERACTIONS

Patients who are administered local anesthetics are at increased risk of developing methemoglobinemia when concurrently exposed to the following drugs, which could include other local anesthetics [see Warnings and Precautions (5.4)]:

Examples of Drugs Associated with Methemoglobinemia
Class | Examples
Nitrates/Nitrites | nitric oxide, nitroglycerin, nitroprusside, nitrous oxide
Local anesthetics | articaine, benzocaine, bupivacaine, lidocaine, mepivacaine, prilocaine, procaine, ropivacaine, tetracaine
Antineoplastic agents | cyclophosphamide, flutamide, hydroxyurea, ifosfamide, rasburicase
Antibiotics | dapsone, nitrofurantoin, para-aminosalicylic acid, sulfonamides
Antimalarials | chloroquine, primaquine
Anticonvulsants | Phenobarbital, phenytoin, sodium valproate
Other drugs | acetaminophen, metoclopramide, quinine, sulfasalazine

NAROPIN should be used with caution in patients receiving other local anesthetics or agents structurally related to amide- type local anesthetics, since the toxic effects of these drugs are additive. Cytochrome P4501A2 is involved in the formation of 3-hydroxy ropivacaine, the major metabolite. In vivo, the plasma clearance of ropivacaine was reduced by 70% during coadministration of fluvoxamine (25 mg bid for 2 days), a selective and potent CYP1A2 inhibitor. Thus strong inhibitors of cytochrome P4501A2, such as fluvoxamine, given concomitantly during administration of NAROPIN, can interact with NAROPIN leading to increased ropivacaine plasma levels. Caution should be exercised when CYP1A2 inhibitors are coadministered. Possible interactions with drugs known to be metabolized by CYP1A2 via competitive inhibition such as theophylline and imipramine may also occur. Coadministration of a selective and potent inhibitor of CYP3A4, ketoconazole (100 mg bid for 2 days with ropivacaine infusion administered 1 hour after ketoconazole) caused a 15% reduction in in vivo plasma clearance of ropivacaine.

Specific trials studying the interaction between ropivacaine and class III antiarrhythmic drugs (e.g., amiodarone) have not been performed, but caution is advised [see Warnings and Precautions (5.13)].

8 USE IN SPECIFIC POPULATIONS

8.1 Pregnancy

Risk Summary

There are no available human data on use of Naropin (ropivacaine) Injection in pregnant women to evaluate a drug-associated risk of major birth defects, miscarriage, or other adverse maternal or fetal outcomes. Local anesthetics may cause varying degrees of toxicity to the mother and fetus and adverse reactions include alterations of the central nervous system, peripheral vascular tone, and cardiac function (see Clinical Considerations). No teratogenicity was observed at doses up to 0.3 times the maximum recommended human dose of 770 mg/24 hours for epidural use, and equal to the MRHD of 250 mg for nerve block use, based on body surface area (BSA) comparisons and a 60 kg human weight (see Animal data).

The estimated background risk of major birth defects and miscarriage for the indicated population is unknown. All pregnancies have a background risk of birth defect, loss, or other adverse outcomes. In the U. S. general population, the estimated background risk of major birth defects and miscarriage in clinically recognized pregnancies is 2% to 4% and 15% to 20%, respectively.

Clinical Considerations

Labor or Delivery

Local anesthetics, including ropivacaine, rapidly cross the placenta, and when used for epidural block can cause varying degrees of maternal, fetal, and neonatal toxicity [see Clinical Pharmacology (12)]. The incidence and degree of toxicity depend upon the procedure performed, the type and amount of drug used, and the technique of drug administration. Adverse reactions in the parturient, fetus and neonate involve alterations of the central nervous system, peripheral vascular tone and cardiac function.

Maternal Adverse reactions

Maternal hypotension has resulted from regional anesthesia. Local anesthetics produce vasodilation by blocking sympathetic nerves. Therefore, during treatment of systemic toxicity, maternal hypotension or fetal bradycardia following regional block, the parturient should be maintained in the left lateral decubitus position if possible, or manual displacement of the uterus off the great vessels be accomplished. Elevating the patient's legs will also help prevent decreases in blood pressure. The fetal heart rate also should be monitored continuously, and electronic fetal monitoring is highly advisable.

Data

Animal data

No malformations were reported in embryo-fetal development toxicity studies conducted in pregnant New Zealand white rabbits and Sprague-Dawley rats. During gestation days 6 to 18, rabbits received daily subcutaneous doses of ropivacaine at 1.3, 4.2, or 13 mg/kg/day (equivalent to 0.03, 0.10, and 0.33 times the maximum recommended human dose (MRHD) of 770 mg/24 hours, respectively, and 0.10, 0.32, and 1.0 times the MRHD of 250 mg for nerve block use, respectively based on body surface area (BSA) comparisons and a 60 kg human weight). Rats received daily subcutaneous doses of 5.3, 11, and 26 mg/kg/day (equivalent to 0.07, 0.14, and 0.33 times the MRHD for epidural use, respectively, and 0.21, 0.43, and 1.0 times the MRHD for nerve block use, respectively, based on BSA comparisons) during GD 6 to 15.

No treatment-related effects on late fetal development, parturition, litter size, lactation, neonatal viability, or growth of the offspring were reported in a prenatal and postnatal reproductive and development toxicity study; however functional endpoints were not evaluated. Female rats were dosed daily subcutaneously from GD 15 to Lactation Day 20 at doses of 5.3, 11,and 26 mg/kg/day (equivalent to 0.07, 0.1, and 0.3 times the MRHD for epidural use, respectively, and 0.21, 0.43, and 1.0 times the MRHD for nerve block use, respectively), with maternal toxicity exhibited at the high dose.

No adverse effects in physical developmental milestones or in behavioral tests were reported in a 2-generational reproduction study, in which rats received daily subcutaneous doses of 6.3, 12, and 23 mg/kg/day (equivalent to 0.08, 0.15, and 0.29 times the MRHD for epidural use, respectively, and 0.24, 0.45, and 0.88 times the MRHD for nerve block use, respectively, based on BSA comparisons) for 9 weeks before mating and during mating for males, and for 2 weeks before mating and during mating, pregnancy, and lactation, up to day 42 post coitus for females. Significant pup loss was observed in the high dose group during the first 3 days postpartum, from a few hours up to 3 days after delivery compared to the control group, which was considered secondary to impaired maternal care due to maternal toxicity. No differences were observed in litter parameters, or fertility, mean gestation time, or number of live births were observed between the control (saline) and treatment groups [see Carcinogenesis, Mutagenesis, Impairment of Fertility (13.1)].

8.2 Lactation

Risk Summary

One publication reported that ropivacaine is present in human milk at low levels following administration of ropivacaine in women undergoing cesarean section. No adverse reactions were reported in the infants. There is no available information on the drug's effects on milk production. The developmental and health benefits of breastfeeding should be considered along with the mother's clinical need for NAROPIN and any potential adverse effects on the breastfed child from NAROPIN or from the underlying maternal condition.

8.4 Pediatric Use

The safety and efficacy of NAROPIN in pediatric patients have not been established.

8.5 Geriatric Use

Of the 2,978 subjects that were administered NAROPIN Injection in 71 controlled and uncontrolled clinical studies, 803 patients (27%) were 65 years of age or older which includes 127 patients (4%) 75 years of age and over. NAROPIN Injection was found to be safe and effective in the patients in these studies. Clinical data in one published article indicate that differences in various pharmacodynamic measures were observed with increasing age. In one study, the upper level of analgesia increased with age, the maximum decrease of mean arterial pressure (MAP) declined with age during the first hour after epidural administration, and the intensity of motor blockade increased with age.

This drug and its metabolites are known to be excreted by the kidney, and the risk of toxic reactions to this drug may be greater in patients with impaired renal function. Elderly patients are more likely to have decreased hepatic, renal, or cardiac function, as well as concomitant disease. Therefore, care should be taken in dose selection, starting at the low end of the dosage range, and it may be useful to monitor renal function [see Clinical Pharmacology (12.3)].

8.6 Hepatic Impairment

Because amide-type local anesthetics such as ropivacaine are metabolized by the liver, these drugs, especially repeat doses, should be used cautiously in patients with hepatic disease. Patients with severe hepatic disease, because of their inability to metabolize local anesthetics normally, are at a greater risk of developing toxic plasma concentrations [see Warning and Precautions (5.11)].

8.7 Renal Impairment

This drug and its metabolites are known to be excreted by the kidney, and the risk of toxic reactions to this drug may be greater in patients with impaired renal function. Therefore, care should be taken in dose selection, starting at the low end of the dosage range, and it may be useful to monitor renal function [see Clinical Pharmacology (12.3)].

10 OVERDOSAGE

Acute emergencies from local anesthetics are generally related to high plasma levels encountered, or large doses administered, during therapeutic use of local anesthetics or to unintended subarachnoid or intravascular injection of local anesthetic solution [see Adverse Reactions (6) and Warnings and Precautions (5.1, 5.2, 5.6)].

10.1 Treatment

Therapy with NAROPIN should be discontinued at the first sign of toxicity. No specific information is available for the treatment of toxicity with NAROPIN; therefore, treatment should be symptomatic and supportive. The first consideration is prevention, best accomplished by incremental injection of NAROPIN, careful and constant monitoring of cardiovascular and respiratory vital signs and the patient's state of consciousness after each local anesthetic and during continuous infusion. At the first sign of change in mental status, oxygen should be administered.

The first step in the management of systemic toxic reactions, as well as underventilation or apnea due to unintentional subarachnoid injection of drug solution, consists of immediate attention to the establishment and maintenance of a patent airway and effective assisted or controlled ventilation with 100% oxygen with a delivery system capable of permitting immediate positive airway pressure by mask. Circulation should be assisted as necessary. This may prevent convulsions if they have not already occurred.

If necessary, use drugs to control convulsions. Intravenous barbiturates, anticonvulsant agents, or muscle relaxants should only be administered by those familiar with their use. Immediately after the institution of these ventilatory measures, the adequacy of the circulation should be evaluated. Supportive treatment of circulatory depression may require administration of intravenous fluids, and, when appropriate, a vasopressor dictated by the clinical situation (such as ephedrine or epinephrine to enhance myocardial contractile force).

Should cardiac arrest occur, prolonged resuscitative efforts may be required to improve the probability of a successful outcome.

The mean dosages of ropivacaine producing seizures, after intravenous infusion in dogs, nonpregnant and pregnant sheep were 4.9, 6.1 and 5.9 mg/kg, respectively. These doses were associated with peak arterial total plasma concentrations of 11.4, 4.3 and 5 mcg/mL, respectively.

In human volunteers given intravenous NAROPIN, the mean (min-max) maximum tolerated total and free arterial plasma concentrations were 4.3 (3.4 to 5.3) and 0.6 (0.3 to 0.9) mcg/mL respectively, at which time moderate CNS symptoms (muscle twitching) were noted.

Clinical data from patients experiencing local anesthetic induced convulsions demonstrated rapid development of hypoxia, hypercarbia and acidosis within a minute of the onset of convulsions. These observations suggest that oxygen consumption and carbon dioxide production are greatly increased during local anesthetic convulsions and emphasize the importance of immediate and effective ventilation with oxygen which may avoid cardiac arrest.

If difficulty is encountered in the maintenance of a patent airway or if prolonged ventilatory support (assisted or controlled) is indicated, endotracheal intubation, employing drugs and techniques familiar to the clinician, may be indicated after initial administration of oxygen by mask.

The supine position is dangerous in pregnant women at term because of aortocaval compression by the gravid uterus. Therefore, during treatment of systemic toxicity, maternal hypotension or fetal bradycardia following regional block, the parturient should be maintained in the left lateral decubitus position if possible, or manual displacement of the uterus off the great vessels should be accomplished. Resuscitation of obstetrical patients may take longer than resuscitation of non-pregnant patients and closed-chest cardiac compression may be ineffective. Rapid delivery of the fetus may improve the response to resuscitative efforts.

11 DESCRIPTION

NAROPIN® Injection is a sterile, isotonic solution that contains ropivacaine hydrochloride as the active pharmaceutical ingredient. Ropivacaine hydrochloride is a member of the amino amide class of local anesthetics. NAROPIN® Injection is administered parenterally by for infiltration, epidural, and nerve block.

Ropivacaine hydrochloride is chemically described as S-(-)-1-propyl-2',6'-pipecoloxylidide hydrochloride monohydrate. The drug substance is a white crystalline powder, with the following structural formula:

C 17 H 26 N 2 O•HCl•H 2 O

M.W. 328.89

At 25 °C ropivacaine hydrochloride has a solubility of 53.8 mg/mL in water, a distribution ratio between n-octanol and phosphate buffer at pH 7.4 of 14:1 and a pKa of 8.07 in 0.1 M KCl solution. The pKa of ropivacaine is approximately the same as bupivacaine (8.1) and is similar to that of mepivacaine (7.7). However, ropivacaine has an intermediate degree of lipid solubility compared to bupivacaine and mepivacaine.

NAROPIN (ropivacaine hydrochloride) injection is a clear, colorless, and preservative-free solution. Each mL contains 2.1 mg, 5.3 mg, 7.9 mg or 10.6 mg ropivacaine hydrochloride monohydrate (equivalent to 2.0 mg, 5.0 mg, 7.5 mg or 10 mg of ropivacaine hydrochloride anhydrous), and 8.6 mg, 8.0 mg, 7.5 mg or 7.1 mg of sodium chloride; respectively, and sodium hydroxide and hydrochloric acid as pH adjusters, in water for injection. The pH is adjusted between 4.0 to 6.0. The specific gravity of NAROPIN Injection solutions range from 1.002 to 1.005 at 25°C.

12 CLINICAL PHARMACOLOGY

12.1 Mechanism of Action

Ropivacaine is a member of the amino amide class of local anesthetics and is supplied as the pure S-(-)-enantiomer. Local anesthetics block the generation and the conduction of nerve impulses, presumably by increasing the threshold for electrical excitation in the nerve, by slowing the propagation of the nerve impulse, and by reducing the rate of rise of the action potential. In general, the progression of anesthesia is related to the diameter, myelination and conduction velocity of affected nerve fibers. Clinically, the order of loss of nerve function is as follows: (1) pain, (2) temperature, (3) touch, (4) proprioception, and (5) skeletal muscle tone.

12.2 Pharmacodynamics

Studies in humans have demonstrated that, unlike most other local anesthetics, the presence of epinephrine has no major effect on either the time of onset or the duration of action of ropivacaine. Likewise, addition of epinephrine to ropivacaine has no effect on limiting systemic absorption of ropivacaine.

Systemic absorption of local anesthetics can produce effects on the central nervous and cardiovascular systems. At blood concentrations achieved with therapeutic doses, changes in cardiac conduction, excitability, refractoriness, contractility, and peripheral vascular resistance have been reported. Toxic blood concentrations depress cardiac conduction and excitability, which may lead to atrioventricular block, ventricular arrhythmias and to cardiac arrest, sometimes resulting in fatalities. In addition, myocardial contractility is depressed and peripheral vasodilation occurs, leading to decreased cardiac output and arterial blood pressure.

Following systemic absorption, local anesthetics can produce central nervous system stimulation, depression or both. Apparent central stimulation is usually manifested as restlessness, tremors and shivering, progressing to convulsions, followed by depression and coma, progressing ultimately to respiratory arrest. However, the local anesthetics have a primary depressant effect on the medulla and on higher centers. The depressed stage may occur without a prior excited stage.

In 2 clinical pharmacology studies (total n=24) ropivacaine and bupivacaine were infused (10 mg/min) in human volunteers until the appearance of CNS symptoms, e.g., visual or hearing disturbances, perioral numbness, tingling and others. Similar symptoms were seen with both drugs. In 1 study, the mean ± SD maximum tolerated intravenous dose of ropivacaine infused (124 ± 38 mg) was significantly higher than that of bupivacaine (99 ± 30 mg) while in the other study the doses were not different (115 ± 29 mg of ropivacaine and 103 ± 30 mg of bupivacaine). In the latter study, the number of subjects reporting each symptom was similar for both drugs with the exception of muscle twitching which was reported by more subjects with bupivacaine than ropivacaine at comparable intravenous doses. At the end of the infusion, ropivacaine in both studies caused significantly less depression of cardiac conductivity (less QRS widening) than bupivacaine. Ropivacaine and bupivacaine caused evidence of depression of cardiac contractility, but there were no changes in cardiac output.

Clinical data in one published article indicate that differences in various pharmacodynamic measures were observed with increasing age. In one study, the upper level of analgesia increased with age, the maximum decrease of mean arterial pressure (MAP) declined with age during the first hour after epidural administration, and the intensity of motor blockade increased with age. However, no pharmacokinetic differences were observed between elderly and younger patients.

In non-clinical pharmacology studies comparing ropivacaine and bupivacaine in several animal species, the cardiac toxicity of ropivacaine was less than that of bupivacaine, although both were considerably more toxic than lidocaine.

Arrhythmogenic and cardio-depressant effects were seen in animals at significantly higher doses of ropivacaine than bupivacaine. The incidence of successful resuscitation was not significantly different between the ropivacaine and bupivacaine groups.

12.3 Pharmacokinetics

Absorption

The systemic concentration of ropivacaine is dependent on the total dose and concentration of drug administered, the route of administration, the patient's hemodynamic/circulatory condition, and the vascularity of the administration site.

From the epidural space, ropivacaine shows complete and biphasic absorption. The half-lives of the 2 phases, (mean ± SD) are 14 ± 7 minutes and 4.2 ± 0.9 h, respectively. The slow absorption is the rate limiting factor in the elimination of ropivacaine that explains why the terminal half-life is longer after epidural than after intravenous administration.

Ropivacaine shows dose-proportionality up to the highest intravenous dose studied, 80 mg, corresponding to a mean ± SD peak plasma concentration of 1.9 ± 0.3 mcg/mL.

Table 7 Pharmacokinetic (Plasma Concentration-Time) Data From Clinical Trials
Route | Epidural Infusion* |  | Epidural Infusion* | Epidural Block† | Epidural Block† | Plexus Block‡ | IV Infusion§
Dose (mg) | 1493 ± 10 | 2075 ± 206 | 1217 ± 277 | 150 | 187.5 | 300 | 40
N | 12 | 12 | 11 | 8 | 8 | 10 | 12
Cmax (mg/L) | 2.4 ± 1¶ | 2.8 ± 0.5¶ | 2.3 ± 1.1¶ | 1.1 ± 0.2 | 1.6 ± 0.6 | 2.3 ± 0.8 | 1.2 ± 0.2#
Tmax (min) | n/a♠ | n/a | n/a | 43 ± 14 | 34 ± 9 | 54 ± 22 | n/a
AUC0- (mg.h/L) | 135.5 ± 50 | 145 ± 34 | 161 ± 90 | 7.2 ± 2 | 11.3 ± 4 | 13 ± 3.3 | 1.8 ± 0.6
CL (L/h) | 11.03 | 13.7 | n/a | 5.5 ± 2 | 5 ± 2.6 | n/a | 21.2 ± 7
t1/2 (hr) ♥ | 5 ± 2.5 | 5.7 ± 3 | 6 ± 3 | 5.7 ± 2 | 7.1 ± 3 | 6.8 ± 3.2 | 1.9 ± 0.5
* Continuous 72 hour epidural infusion after an epidural block with 5 or 10 mg/mL.
† Epidural anesthesia with 7.5 mg/mL (0.75%) for cesarean delivery.
‡ Brachial plexus block with 7.5 mg/mL (0.75%) ropivacaine.
§ 20 minute IV infusion to volunteers (40 mg).
¶ Cmax measured at the end of infusion (i.e., at 72 hr).
# Cmax measured at the end of infusion (i.e., at 20 minutes).
♠ n/a=not applicable
♥ t½ is the true terminal elimination half-life. On the other hand, t½ follows absorption dependent elimination (flip-flop) after non-intravenous administration.

In some patients after a 300 mg dose for brachial plexus block, free plasma concentrations of ropivacaine may approach the threshold for CNS toxicity [see Warnings and Precautions (5.7)]. At a dose of greater than 300 mg, for local infiltration, the terminal half-life may be longer (>30 hours).

Distribution

After intravascular infusion, ropivacaine has a steady-state volume of distribution of 41 ± 7 liters. Ropivacaine is 94% protein bound, mainly to α1-acid glycoprotein. An increase in total plasma concentrations during continuous epidural infusion has been observed, related to a postoperative increase of α1-acid glycoprotein. Variations in unbound, i.e., pharmacologically active, concentrations have been less than in total plasma concentration. Ropivacaine readily crosses the placenta and equilibrium in regard to unbound concentration will be rapidly reached [see Warnings and Precautions (5) and Use in Specific Population (8.1)].

Metabolism

Ropivacaine is extensively metabolized in the liver, predominantly by aromatic hydroxylation mediated by cytochrome P4501A to 3-hydroxy ropivacaine. After a single IV dose approximately 37% of the total dose is excreted in the urine as both free and conjugated 3-hydroxy ropivacaine. Low concentrations of 3-hydroxy ropivacaine have been found in the plasma. Urinary excretion of the 4 hydroxy ropivacaine, and both the 3-hydroxy N de alkylated (3-OH-PPX) and 4-hydroxy N-de-alkylated (4-OH-PPX) metabolites account for less than 3% of the dose. An additional metabolite, 2-hydroxy-methyl- ropivacaine, has been identified but not quantified in the urine. The N-de-alkylated metabolite of ropivacaine (PPX) and 3- OH-ropivacaine are the major metabolites excreted in the urine during epidural infusion. Total PPX concentration in the plasma was about half as that of total ropivacaine; however, mean unbound concentrations of PPX were about 7 to 9 times higher than that of unbound ropivacaine following continuous epidural infusion up to 72 hours. Unbound PPX, 3-hydroxy and 4-hydroxy ropivacaine, have a pharmacological activity in animal models less than that of ropivacaine. There is no evidence of in vivo racemization in urine of ropivacaine.

Elimination

The kidney is the main excretory organ for most local anesthetic metabolites. In total, 86% of the ropivacaine dose is excreted in the urine after intravenous administration of which only 1% relates to unchanged drug. After intravenous administration ropivacaine has a mean ± SD total plasma clearance of 387 ± 107 mL/min, an unbound plasma clearance of 7.2 ± 1.6 L/min, and a renal clearance of 1 mL/min. The mean ± SD terminal half-life is 1.8 ± 0.7 h after intravascular administration and 4.2 ± 1 h after epidural administration.

13 NONCLINICAL TOXICOLOGY

13.1 Carcinogenesis, Mutagenesis, Impairment of Fertility

Carcinogenesis

Long-term studies in animals to evaluate the carcinogenic potential of ropivacaine have not been conducted.

Mutagenesis

Weak mutagenic activity was seen in the mouse lymphoma test. However, ropivacaine was negative in an in vitro Ames assay and an in vivo mouse micronucleus assay.

Impairment of Fertility

No adverse effects on fertility or early embryonic development were reported in a 2-generational reproduction study in which female rats (F0) were administered subcutaneous doses of 6.3, 12, and 23 mg/kg/day (equivalent to 0.08, 0.15, and 0.29 times the maximum recommended human dose (MRHD) of 770 mg/24 hours for epidural use, respectively, and 0.24, 0.45, and 0.88 times the MRHD of 250 mg for nerve block use, respectively, based on BSA comparisons and a 60 kg human) throughout the mating period and pregnancy, partus, and lactation.

13.2 Animal Toxicology and/or Pharmacology

The mean dosages of ropivacaine producing seizures, after intravenous infusion in dogs, nonpregnant and pregnant sheep were 4.9, 6.1 and 5.9 mg/kg (HED: 5.3, 6.6, and 6.4 mg/kg, based on 75 kg sheep weight and 60 kg human weight), respectively. These doses were associated with peak arterial total plasma concentrations of 11.4, 4.3 and 5 mcg/mL, respectively.

14 CLINICAL STUDIES

Ropivacaine was studied as a local anesthetic both for surgical anesthesia and for acute pain management [see Dosage and Administration (2)].

The onset, depth and duration of sensory block are, in general, similar to bupivacaine. However, the depth and duration of motor block, in general, are less than that with bupivacaine.

14.1 Epidural Administration in Surgery

There were 25 clinical studies performed in 900 patients to evaluate NAROPIN epidural injection for general surgery. NAROPIN was used in doses ranging from 75 to 250 mg. In doses of 100 to 200 mg, the median (1st to 3rd quartile) onset time to achieve a T10 sensory block was 10 (5 to 13) minutes and the median (1st to 3rd quartile) duration at the T10 level was 4 (3 to 5) hours [see Dosage and Administration (2.2)]. Higher doses produced a more profound block with a greater duration of effect.

14.2 Epidural Administration in Cesarean Section

A total of 12 studies were performed with epidural administration of NAROPIN for cesarean section. Eight of these studies involved 218 patients using the concentration of 5 mg/mL (0.5%) in doses up to 150 mg. Median onset measured at T6 ranged from 11 to 26 minutes. Median duration of sensory block at T6 ranged from 1.7 to 3.2 h, and duration of motor block ranged from 1.4 to 2.9 h. NAROPIN provided adequate muscle relaxation for surgery in all cases.

In addition, 4 active controlled studies for cesarean section were performed in 264 patients at a concentration of 7.5 mg/mL (0.75%) in doses up to 187.5 mg. Median onset measured at T6 ranged from 4 to 15 minutes. Seventy-seven to 96% of NAROPIN-exposed patients reported no pain at delivery. Some patients received other anesthetic, analgesic, or sedative modalities during the course of the operative procedure.

14.3 Epidural Administration in Labor and Delivery

A total of 9 double-blind clinical studies, involving 240 patients were performed to evaluate NAROPIN for epidural block for management of labor pain. When administered in doses up to 278 mg as intermittent injections or as a continuous infusion, NAROPIN produced adequate pain relief.

A prospective meta-analysis on 6 of these studies provided detailed evaluation of the delivered newborns and showed no difference in clinical outcomes compared to bupivacaine. There were significantly fewer instrumental deliveries in mothers receiving ropivacaine as compared to bupivacaine.

Table 8 Labor and Delivery Meta-analysis: Mode of Delivery
Delivery Mode | NAROPIN n = 199 |  | Bupivacaine n = 188
 | n | % | n | %
Spontaneous Vertex | 116 | 58 | 92 | 49
Vacuum Extractor | 26 |  | 33
 |  | }27* |  | }40
Forceps | 28 |  | 42
Cesarean Section | 29 | 15 | 21 | 11
*p=0.004 versus bupivacaine

14.4 Epidural Administration in Postoperative Pain Management

There were 8 clinical studies performed in 382 patients to evaluate NAROPIN 2 mg/mL (0.2%) for postoperative pain management after upper and lower abdominal surgery and after orthopedic surgery. The studies utilized intravascular morphine via PCA as a rescue medication and quantified as an efficacy variable.

Epidural anesthesia with NAROPIN 5 mg/mL, (0.5%) was used intraoperatively for each of these procedures prior to initiation of postoperative NAROPIN. The incidence and intensity of the motor block were dependent on the dose rate of NAROPIN and the site of injection. Cumulative doses of up to 770 mg of ropivacaine were administered over 24 hours (intraoperative block plus postoperative continuous infusion). The overall quality of pain relief, as judged by the patients, in the ropivacaine groups was rated as good or excellent (73% to 100%). The frequency of motor block was greatest at 4 hours and decreased during the infusion period in all groups. At least 80% of patients in the upper and lower abdominal studies and 42% in the orthopedic studies had no motor block at the end of the 21-hour infusion period. Sensory block was also dose rate dependent and a decrease in spread was observed during the infusion period.

A double-blind, randomized, clinical trial compared lumbar epidural infusion of NAROPIN (n=26) and bupivacaine (n=26) at 2 mg/mL (8 mL/h), for 24 hours after knee replacement. In this study, the pain scores were higher in the NAROPIN group, but the incidence and the intensity of motor block were lower.

Continuous epidural infusion of NAROPIN 2 mg/mL (0.2%) during up to 72 hours for postoperative pain management after major abdominal surgery was studied in 2 multicenter, double-blind studies. A total of 391 patients received a low thoracic epidural catheter, and NAROPIN 7.5 mg/L (0.75%) was given for surgery, in combination with GA. Postoperatively, NAROPIN 2 mg/mL (0.2%), 4 to 14 mL/h, alone or with fentanyl 1, 2, or 4 mcg/mL was infused through the epidural catheter and adjusted according to the patient's needs. These studies support the use of NAROPIN 2 mg/mL (0.2%) for epidural infusion at 6 to 14 mL/h (12 to 28 mg) for up to 72 hours and demonstrated adequate analgesia with only slight and nonprogressive motor block in cases of moderate to severe postoperative pain.

Clinical studies with 2 mg/mL (0.2%) NAROPIN have demonstrated that infusion rates of 6 to 14 mL (12 to 28 mg) per hour provide adequate analgesia with nonprogressive motor block in cases of moderate to severe postoperative pain. In these studies, this technique resulted in a significant reduction in patients' morphine rescue dose requirement. Clinical experience supports the use of NAROPIN epidural infusions for up to 72 hours.

14.5 Peripheral Nerve Block

NAROPIN, 5 mg/mL (0.5%), was evaluated for its ability to provide anesthesia for surgery using the techniques of Peripheral Nerve Block. There were 13 studies performed including a series of 4 pharmacodynamic and pharmacokinetic studies performed on minor nerve blocks. From these, 235 NAROPIN-treated patients were evaluable for efficacy.

NAROPIN was used in doses up to 275 mg. When used for brachial plexus block, onset depended on technique used. Supraclavicular blocks were consistently more successful than axillary blocks. The median onset of sensory block (anesthesia) produced by ropivacaine 0.5% via axillary block ranged from 10 minutes (medial brachial cutaneous nerve) to 45 minutes (musculocutaneous nerve). Median duration ranged from 3.7 hours (medial brachial cutaneous nerve) to 8.7 hours (ulnar nerve). The 5 mg/mL (0.5%) NAROPIN solution gave success rates from 56% to 86% for axillary blocks, compared with 92% for supraclavicular blocks.

In addition, NAROPIN, 7.5 mg/mL (0.75%), was evaluated in 99 NAROPIN-treated patients, in 2 double-blind studies, performed to provide anesthesia for surgery using the techniques of Brachial Plexus Block. NAROPIN 7.5 mg/mL was compared to bupivacaine 5 mg/mL. In 1 study, patients underwent axillary brachial plexus block using injections of 40 mL (300 mg) of NAROPIN, 7.5 mg/mL (0.75%) or 40 mL injections of bupivacaine, 5 mg/mL (200 mg). In a second study, patients underwent subclavian perivascular brachial plexus block using 30 mL (225 mg) of NAROPIN, 7.5 mg/mL (0.75%) or 30 mL of bupivacaine 5 mg/mL (150 mg). There was no significant difference between the NAROPIN and bupivacaine groups in either study with regard to onset of anesthesia, duration of sensory blockade, or duration of anesthesia.

The median duration of anesthesia varied between 11.4 and 14.4 hours with both techniques. In one study, using the axillary technique, the quality of analgesia and muscle relaxation in the NAROPIN group was judged to be significantly superior to bupivacaine by both investigator and surgeon. However, using the subclavian perivascular technique, no statistically significant difference was found in the quality of analgesia and muscle relaxation as judged by both the investigator and surgeon. The use of NAROPIN 7.5 mg/mL for block of the brachial plexus via either the subclavian perivascular approach using 30 mL (225 mg) or via the axillary approach using 40 mL (300 mg) both provided effective and reliable anesthesia.

14.6 Local Infiltration

A total of 7 clinical studies were performed to evaluate the local infiltration of NAROPIN to produce anesthesia for surgery and analgesia in postoperative pain management. In these studies 297 patients who received NAROPIN in doses up to 200 mg (concentrations up to 5 mg/mL, 0.5%) were evaluable for efficacy. With infiltration of 100 to 200 mg NAROPIN, the time to first request for analgesic was 2 to 6 hours. When compared to placebo, NAROPIN produced lower pain scores and a reduction of analgesic consumption.

16 How Supplied/Storage and Handling

NAROPIN (ropivacaine hydrochloride) Injection is a clear colorless, and preservative-free solution, available in single-dose containers in 2 mg/mL (0.2%) and 5 mg/mL (0.5%) concentrations.

Storage

Solutions should be stored at 20ºC to 25°C (68ºF to 77°F); excursions permitted to 15°C to 30°C (59°F to 86°F) [see USP Controlled Room Temperature].

NAROPIN® Single-Dose Vials
Product Code | Unit of Sale | Strength | Each
PRX278523 | NDC 63323-285-28 Unit of 25 | 0.2% 40 mg per 20 mL (2 mg per mL) | NDC 63323-285-41 20 mL Single-Dose Vial
PRX278623 | NDC 63323-286-27 Unit of 25 | 0.5% 100 mg per 20 mL (5 mg per mL) | NDC 63323-286-41 20 mL Single-Dose Vial
PRX278635 | NDC 63323-286-38 Unit of 25 | 0.5% 150 mg per 30 mL (5 mg per mL) | NDC 63323-286-43 30 mL Single-Dose Vial

NAROPIN® Single-Dose Infusion Bottles
Product Code | Unit of Sale | Strength | Each
PRX278565 | NDC 63323-285-68 Unit of 12 | 0.2% 200 mg per 100 mL (2 mg per mL) | NDC 63323-285-53 100 mL Single-Dose Infusion Bottle
PRX278564 | NDC 63323-285-73 Unit of 12 | 0.2% 400 mg per 200 mL (2 mg per mL) | NDC 63323-285-59 200 mL Single-Dose Infusion Bottle

For single-dose vials: Discard unused portion.

NAROPIN container closure is not made with natural rubber latex.

17 PATIENT COUNSELING INFORMATION

17.1 Information for Patients and Caregivers

When appropriate, patients should be informed in advance that they may experience temporary loss of sensation and motor activity in the anesthetized part of the body following proper administration of lumbar epidural anesthesia. Also, when appropriate, the physician should discuss other information including adverse reactions in the NAROPIN package insert.

Inform patients that use of local anesthetics may cause methemoglobinemia, a serious condition that must be treated promptly. Advise patients or caregivers to seek immediate medical attention if they or someone in their care experience the following signs or symptoms: pale, gray, or blue colored skin (cyanosis); headache; rapid heart rate; shortness of breath; lightheadedness; or fatigue.

NAROPIN is a trademark of Fresenius Kabi USA, LLC.

PREMIERProRx® is a registered trademark of Premier Healthcare Alliance, L.P., used under license

Manufactured by:
Fresenius Kabi
Lake Zurich, IL 60047
www.fresenius-kabi.com/us

451350D

PACKAGE LABEL

PACKAGE LABEL - PRINCIPAL DISPLAY - Naropin 100 mL Single Dose Bottle Label

NDC 63323-285-53 PRX278565

Naropin®
(ropivacaine hydrochloride) Injection, USP

0.2% 200 mg per 100 mL
(2 mg per mL)
For Infiltration, Nerve Block, and
Epidural Administration Only.

Not for Intravenous Administration.

Single Dose Only - Discard unused portion.

For continuous infiltration or epidural infusion only.

100 mL

PACKAGE LABEL

PACKAGE LABEL - PRINCIPAL DISPLAY PANEL - Naropin 200 mL Single Dose Bottle Label

NDC 63323-285-59 PRX278564

Naropin®
(ropivacaine hydrochloride) Injection, USP

0.2% 400 mg per 200 mL

(2 mg per mL)

For Infiltration, Nerve Block, and

Epidural Administration Only.

Not for Intravenous Administration.

Single Dose Only – Discard unused portion.

For continuous infiltration or epidural infusion only.

200 mL

PACKAGE LABEL

PACKAGE LABEL - PRINCIPAL DISPLAY - Naropin 30 mL Single Dose Vial Label

NDC 63323-286-43 PRX278635

Naropin®
(ropivacaine hydrochloride) Injection, USP

0.5% 150 mg per 30 mL
(5 mg per mL)
For Infiltration, Nerve Block, and
Epidural Administration Only.

Not for Intravenous Administration.

30 mL Single-Dose Vial

PACKAGE LABEL

PACKAGE LABEL - PRINCIPAL DISPLAY - Naropin 30 mL Single Dose Vial Tray Label

NDC 63323-286-38 PRX278635

Naropin®
(ropivacaine hydrochloride) Injection, USP

0.5% 150 mg per 30 mL
(5 mg per mL)
For Infiltration, Nerve Block, and
Epidural Administration Only.

Not for Intravenous Administration.

Twenty-five 30 mL Single-Dose Vials

PACKAGE LABEL

PACKAGE LABEL - PRINCIPAL DISPLAY PANEL - Naropin 20 mL Single Dose Vial Label

NDC 63323-285-41 PRX278523

Naropin®
(ropivacaine hydrochloride) Injection, USP

0.2% 40 mg per 20 mL

(2 mg per mL)

For Infiltration, Nerve Block, and

Epidural Administration Only.

Not for Intravenous Administration.

20 mL Single-Dose Vial

PACKAGE LABEL

PACKAGE LABEL - PRINCIPAL DISPLAY PANEL - Naropin 20 mL Single Dose Vial Tray Label

NDC 63323-285-28 PRX278523

Naropin®
(ropivacaine hydrochloride) Injection, USP

0.2% 40 mg per 20 mL

(2 mg per mL)

For Infiltration, Nerve Block, and

Epidural Administration Only.

Not for Intravenous Administration.

Twenty-five 20 mL Single-Dose Vials

PACKAGE LABEL

PACKAGE LABEL - PRINCIPAL DISPLAY PANEL - Naropin 20 mL Single Dose Vial Label

NDC 63323-286-41 PRX278623

Naropin®
(ropivacaine hydrochloride) Injection, USP

0.5% 100 mg per 20 mL

(5 mg per mL)

For Infiltration, Nerve Block, and

Epidural Administration Only.

Not for Intravenous Administration.

20 mL Single-Dose Vial

PACKAGE LABEL

PACKAGE LABEL - PRINCIPAL DISPLAY PANEL - Naropin 20 mL Single Dose Vial Tray Label

NDC 63323-286-27 PRX278623

Naropin®
(ropivacaine hydrochloride) Injection, USP

0.5% 100 mg per 20 mL

(5 mg per mL)

For Infiltration, Nerve Block, and

Epidural Administration Only.

Not for Intravenous Administration.

Twenty-five 20 mL Single-Dose Vials